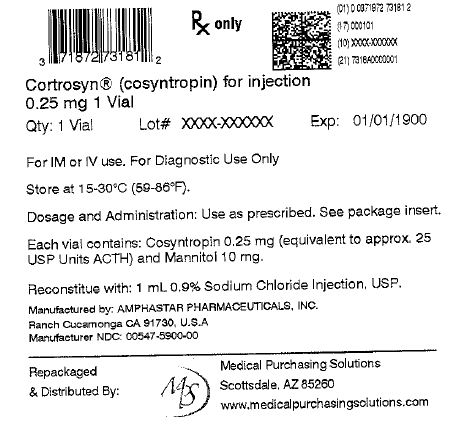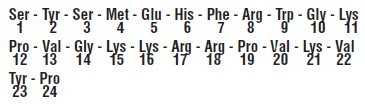 DRUG LABEL: Cortrosyn
NDC: 71872-7318 | Form: INJECTION, POWDER, LYOPHILIZED, FOR SOLUTION
Manufacturer: Medical Purchasing Solutions, LLC
Category: prescription | Type: HUMAN PRESCRIPTION DRUG LABEL
Date: 20240412

ACTIVE INGREDIENTS: COSYNTROPIN 0.25 mg/1 mL
INACTIVE INGREDIENTS: SODIUM CHLORIDE

FOR DIAGNOSTIC USE ONLY

CORTROSYN®

(cosyntropin) for Injection

DESCRIPTION

CORTROSYN®(cosyntropin) for Injection is a sterile lyophilized powder in vials containing 0.25 mg of CORTROSYN®and 10 mg of mannitol to be reconstituted with 1 mL of 0.9% Sodium Chloride Injection, USP. Sodium Hydroxide and Glacial acetic acid may be used to adjust pH. Administration is by intravenous or intramuscular injection. Cosyntropin is α 1 - 24 corticotropin, a synthetic subunit of ACTH. It is an open chain polypeptide containing, from the N terminus, the first 24 of the 39 amino acids of natural ACTH. The sequence of amino acids in the 1 - 24 compound is as follows:

CLINICAL PHARMACOLOGY

CORTROSYN®(cosyntropin) for Injection exhibits the full corticosteroidogenic activity of natural ACTH. Various studies have shown that the biologic activity of ACTH resides in the N-terminal portion of the molecule and that the 1 - 20 amino acid residue is the minimal sequence retaining full activity. Partial or complete loss of activity is noted with progressive shortening of the chain beyond 20 amino acid residue. For example, the decrement from 20 to 19 results in a 70% loss of potency.

The pharmacologic profile of CORTROSYN®is similar to that of purified natural ACTH. It has been established that 0.25 mg of CORTROSYN®will stimulate the adrenal cortex maximally and to the same extent as 25 units of natural ACTH. This dose of CORTROSYN®will produce maximal secretion of 17-OH corticosteroids, 17- ketosteroids and / or 17 - ketogenic steroids.

The extra-adrenal effects which natural ACTH and CORTROSYN®have in common include increased melanotropic activity, increased growth hormone secretion and an adipokinetic effect. These are considered to be without physiological or clinical significance.

Animal, human and synthetic ACTH (1-39) which all contain 39 amino acids exhibit similar immunologic activity. This activity resides in the C-terminal portion of the molecule and the 22-39 amino acid residues exhibit the greatest degree of antigenicity. In contrast, synthetic polypeptides containing 1-19 or fewer amino acids have no detectable immunologic activity. Those containing 1-26, 1-24 or 1-23 amino acids have very little immunologic although full biologic activity. This property of CORTROSYN®assumes added importance in view of the known antigenicity of natural ACTH.

INDICATIONS AND USAGE

CORTROSYN®(cosyntropin) for Injection is intended for use as a diagnostic agent in the screening of patients presumed to have adrenocortical insufficiency. Because of its rapid effect on the adrenal cortex it may be utilized to perform a 30-minute test of adrenal function (plasma cortisol response) as an office or outpatient procedure, using only 2 venipunctures (see DOSAGE AND ADMINISTRATIONsection).

Severe hypofunction of the pituitary - adrenal axis is usually associated with subnormal plasma cortisol values but a low basal level is not per se evidence of adrenal insufficiency and does not suffice to make the diagnosis. Many patients with proven insufficiency will have normal basal levels and will develop signs of insufficiency only when stressed. For this reason a criterion which should be used in establishing the diagnosis is the failure to respond to adequate corticotropin stimulation. When presumptive adrenal insufficiency is diagnosed by a subnormal CORTROSYN®test, further studies are indicated to determine if it is primary or secondary.

Primary adrenal insufficiency (Addison’s disease) is the result of an intrinsic disease process, such as tuberculosis within the gland. The production of adrenocortical hormones is deficient despite high ACTH levels (feedback mechanism). Secondary or relative insufficiency arises as the result of defective production of ACTH leading in turn to disuse atrophy of the adrenal cortex. It is commonly seen, for example, as result of corticosteroid therapy, Sheehan’s syndrome and pituitary tumors or ablation.

The differentiation of both types is based on the premise that a primarily defective gland cannot be stimulated by ACTH whereas a secondarily defective gland is potentially functional and will respond to adequate stimulation with ACTH. Patients selected for further study as the result of a subnormal CORTROSYN®test should be given a 3 or 4 day course of treatment with Repository Corticotropin Injection USP and then retested. Suggested doses are 40 USP units twice daily for 4 days or 60 USP units twice daily for 3 days. Under these conditions little or no increase in plasma cortisol levels will be seen in Addison’s disease whereas higher or even normal levels will be seen in cases with secondary adrenal insufficiency.

CONTRAINDICATIONS

The only contraindication to CORTROSYN®(cosyntropin) for Injection is a history of a previous adverse reaction to it.

PRECAUTIONS

General

CORTROSYN®(cosyntropin) for Injection exhibits slight immunologic activity, does not contain animal protein and is therefore less risky to use than natural ACTH. Patients known to be sensitized to natural ACTH with markedly positive skin tests will, with few exceptions, react negatively when tested intradermally with CORTROSYN®. Most patients with a history of a previous hypersensitivity reaction to natural ACTH or a pre-existing allergic disease will tolerate CORTROSYN®. Despite this however, CORTROSYN®is not completely devoid of immunologic activity and hypersensitivity reactions including rare anaphylaxis are possible. Therefore, the physician should be prepared, prior to injection, to treat any possible acute hypersensitivity reaction.

Drug Interactions

Corticotropin may accentuate the electrolyte loss associated with diuretic therapy.

Carcinogenesis, Mutagenesis, Impairment of Fertility

Long term studies in animals have not been performed to evaluate carcinogenic or mutagenic potential or impairment of fertility. A study in rats noted inhibition of reproductive function like natural ACTH.

Pregnancy

Pregnancy Category C. Animal reproduction studies have not been conducted with CORTROSYN®(cosyntropin) for Injection. It is also not known whether CORTROSYN®can cause fetal harm when administered to a pregnant woman or can affect reproduction capacity. CORTROSYN®should be given to a pregnant woman only if clearly needed.

Nursing Mothers

It is not known whether this drug is excreted in human milk. Because many drugs are excreted in human milk, caution should be exercised when CORTROSYN®(cosyntropin) for Injection is administered to a nursing woman.

Pediatric Use

(See DOSAGE AND ADMINISTRATIONsection.)

ADVERSE REACTIONS

Since CORTROSYN®(cosyntropin) for Injection is intended for diagnostic and not therapeutic use, adverse reactions other than a rare hypersensitivity reaction are not anticipated. A rare hypersensitivity reaction usually associated with a pre-existing allergic disease and/or a previous reaction to natural ACTH is possible. Symptoms may include slight whealing with splotchy erythema at the injection site. There have been rare reports of anaphylactic reaction. The following adverse reactions have been reported in patients after the administration of CORTROSYN®and the association has been neither confirmed nor refuted:

● bradycardia
● tachycardia
● hypertension
● peripheral edema
● rash

DOSAGE AND ADMINISTRATION

CORTROSYN®(cosyntropin) for Injection may be administered intramuscularly or as a direct intravenous injection when used as a rapid screening test of adrenal function. It may also be given as an intravenous infusion over a 4 to 8 hour period to provide a greater stimulus to the adrenal glands. Doses of CORTROSYN®0.25 to 0.75 mg have been used in clinical studies and a maximal response noted with the smallest dose.

A suggested method for a rapid screening test of adrenal function has been described by Wood and Associates (1). A control blood sample of 6 to 7 mL is collected in a heparinized tube. Reconstitute 0.25 mg of CORTROSYN®with 1mL of 0.9% Sodium Chloride Injection, USP to obtain a concentration of 0.25 mg/mL CORTROSYN®and inject intramuscularly. The reconstituted drug product should be inspected visually for particulate matter and discoloration prior to injection. Reconstituted CORTROSYN®should not be retained. In the pediatric population, aged 2 years or less, a dose of 0.125 mg will often suffice. A second blood sample is collected exactly 30 minutes later. Both blood samples should be refrigerated until sent to the laboratory for determination of the plasma cortisol response by some appropriate method. If it is not possible to send them to the laboratory or perform the fluorimetric procedure within 12 hours, then the plasma should be separated and refrigerated or frozen according to need.

Two alternative methods of administration are intravenous injection and infusion. CORTROSYN®can be injected intravenously in 2 to 5 mL of saline over a 2-minute period. When given as an intravenous infusion: CORTROSYN®, 0.25 mg may be added to glucose or saline solutions and given at the rate of approximately 40 micrograms per hour over a 6-hour period. It should not be added to blood or plasma as it is apt to be inactivated by enzymes. Adrenal response may be measured in the usual manner by determining urinary steroid excretion before and after treatment or by measuring plasma cortisol levels before and at the end of the infusion. The latter is preferable because the urinary steroid excretion does not always accurately reflect the adrenal or plasma cortisol response to ACTH.

The usual normal response in most cases is an approximate doubling of the basal level, provided that the basal level does not exceed the normal range. Patients receiving cortisone, hydrocortisone or spironolactone should omit their pre-test doses on the day selected for testing. Patients taking inadvertent doses of cortisone or hydrocortisone on the test day and patients taking spironolactone or women taking drugs which contain estrogen may exhibit abnormally high basal plasma cortisol levels.
A paradoxical response may be noted in the cortisone or hydrocortisone group as seen in a decrease in plasma cortisol values following a stimulating dose of CORTROSYN®.

In the spironolactone or estrogen group only a normal incremental response is to be expected. Many patients with normal adrenal function, however, do not respond to the expected degree so that the following criteria have been established to denote a normal response:

1. The control plasma cortisol level should exceed 5 micrograms/100 mL.
2. The 30-minute level should show an increment of at least 7 micrograms/100 mL above the basal level.
3. The 30-minute level should exceed 18 micrograms/100 mL. Comparable figures have been reported by Greig and co-workers (2).

Plasma cortisol levels usually peak about 45 to 60 minutes after an injection of CORTROSYN®and some prefer the 60-minute interval for testing for this reason. While it is true that the 60-minute values are usually higher than the 30-minute values, the difference may not be significant enough in most cases to outweigh the disadvantage of a longer testing period. If the 60-minute test period is used, the criterion for a normal response is an approximate doubling of the basal plasma cortisol value.

In patients with a raised plasma bilirubin or in patients where the plasma contains free hemoglobin, falsely high fluorescence measurements will result. The test may be performed at any time during the day but because of the physiological diurnal variation of plasma cortisol the criteria listed by Wood cannot apply. It has been shown that basal plasma cortisol levels and the post CORTROSYN®increment exhibit diurnal changes. However, the 30-minute plasma cortisol level remains unchanged throughout the day so that only this single criterion should be used (3).

Parenteral drug products should be inspected visually for particulate matter and discoloration whenever solution and container permit. Reconstituted CORTROSYN®should not be retained.

HOW SUPPLIED

Box of 10 vials of CORTROSYN®(cosyntropin) for Injection 0.25 mg
NDC # 0548-5900-00

Storage

Store at 15-30°C (59-86°F).
CORTROSYN®is intended as a single-dose injection and contains no antimicrobial preservative. Any unused portion should be discarded.

Rx only

REFERENCES

1. Wood, J.B. et al. LANCET 1.243, 1965.
2. Greig, W.R. et al. J. ENDOCR 34.411, 1966.
3. McGill, P.E. et al. ANN RHEUM DIS 26.123, 1967.

Amphastar Pharmaceuticals, Inc.
Rancho Cucamonga, CA 91730 U.S.A. REV. 6-21

PRINCIPLE DISPLAY PANEL - OUTER PACKAGE

For Diagnostic Use Only

CORTROSYN® consyntrosin for Injection

0.25 mg

For IM or IV use

Rx only

NDC 71872-7318-1

Contains 1 Single Dose Vial